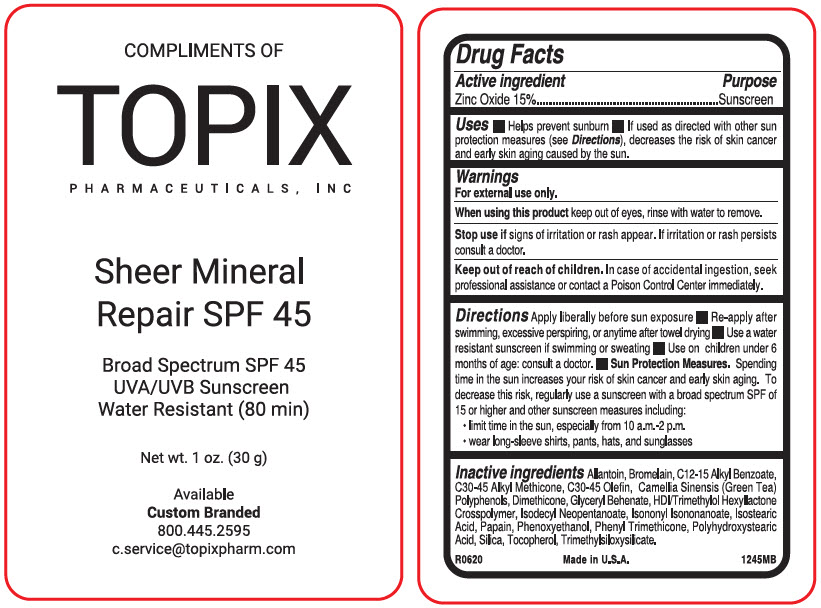 DRUG LABEL: Mineral Repair SPF 45
NDC: 51326-245 | Form: LOTION
Manufacturer: Topiderm, Inc.
Category: otc | Type: HUMAN OTC DRUG LABEL
Date: 20230207

ACTIVE INGREDIENTS: ZINC OXIDE 150 mg/1 g
INACTIVE INGREDIENTS: ALLANTOIN; BROMELAINS; ALKYL (C12-15) BENZOATE; C30-45 ALKYL METHICONE; C30-45 OLEFIN; GREEN TEA LEAF; DIMETHICONE; GLYCERYL MONOBEHENATE; HEXAMETHYLENE DIISOCYANATE/TRIMETHYLOL HEXYLLACTONE CROSSPOLYMER; ISODECYL NEOPENTANOATE; ISONONYL ISONONANOATE; ISOSTEARIC ACID; PAPAIN; PHENOXYETHANOL; PHENYL TRIMETHICONE; POLYHYDROXYSTEARIC ACID (2300 MW); SILICON DIOXIDE; .ALPHA.-TOCOPHEROL; TRIMETHYLSILOXYSILICATE (M/Q 1.0-1.2)

Mineral Repair SPF 45

Drug Facts

Active ingredient

Zinc Oxide 15%

Purpose

Sunscreen

Uses

- Helps prevent sunburn
- If used as directed with other sun protection measures (see Directions), decreases the risk of skin cancer and early skin aging caused by the sun.

Warnings

For external use only.

When using this product keep out of eyes, rinse with water to remove.

Stop use if signs of irritation or rash appear. If irritation or rash persists consult a doctor.

Keep out of reach of children. In case of accidental ingestion, seek professional assistance or contact a Poison Control Center immediately.

Directions

Apply liberally before sun exposure

- Re-apply after swimming, excessive perspiring, or anytime after towel drying
- Use a water resistant sunscreen if swimming or sweating
- Use on children under 6 months of age: consult a doctor.
- Sun Protection Measures. Spending time in the sun increases your risk of skin cancer and early skin aging. To decrease this risk, regularly use a sunscreen with a broad spectrum SPF of 15 or higher and other sunscreen measures including:
  - limit time in the sun, especially from 10 a.m.-2 p.m.
  - wear long-sleeve shirts, pants, hats, and sunglasses

Inactive ingredients

Allantoin, Bromelain, C12-15 Alkyl Benzoate, C30-45 Alkyl Methicone, C30-45 Olefin, Camellia Sinensis (Green Tea) Polyphenols, Dimethicone, Glyceryl Behenate, HDI/Trimethylol Hexyllactone Crosspolymer, Isodecyl Neopentanoate, Isononyl Isononanoate, Isostearic Acid, Papain, Phenoxyethanol, Phenyl Trimethicone, Polyhydroxystearic Acid, Silica, Tocopherol, Trimethylsiloxysilicate.

PRINCIPAL DISPLAY PANEL - 30 g Bottle Label

COMPLIMENTS OF

TOPIX
PHARMACEUTICALS, INC

Sheer Mineral
Repair SPF 45

Broad Spectrum SPF 45
UVA/UVB Sunscreen
Water Resistant (80 min)

Net wt. 1 oz. (30 g)

Available
Custom Branded
800.445.2595
c.service@topixpharm.com